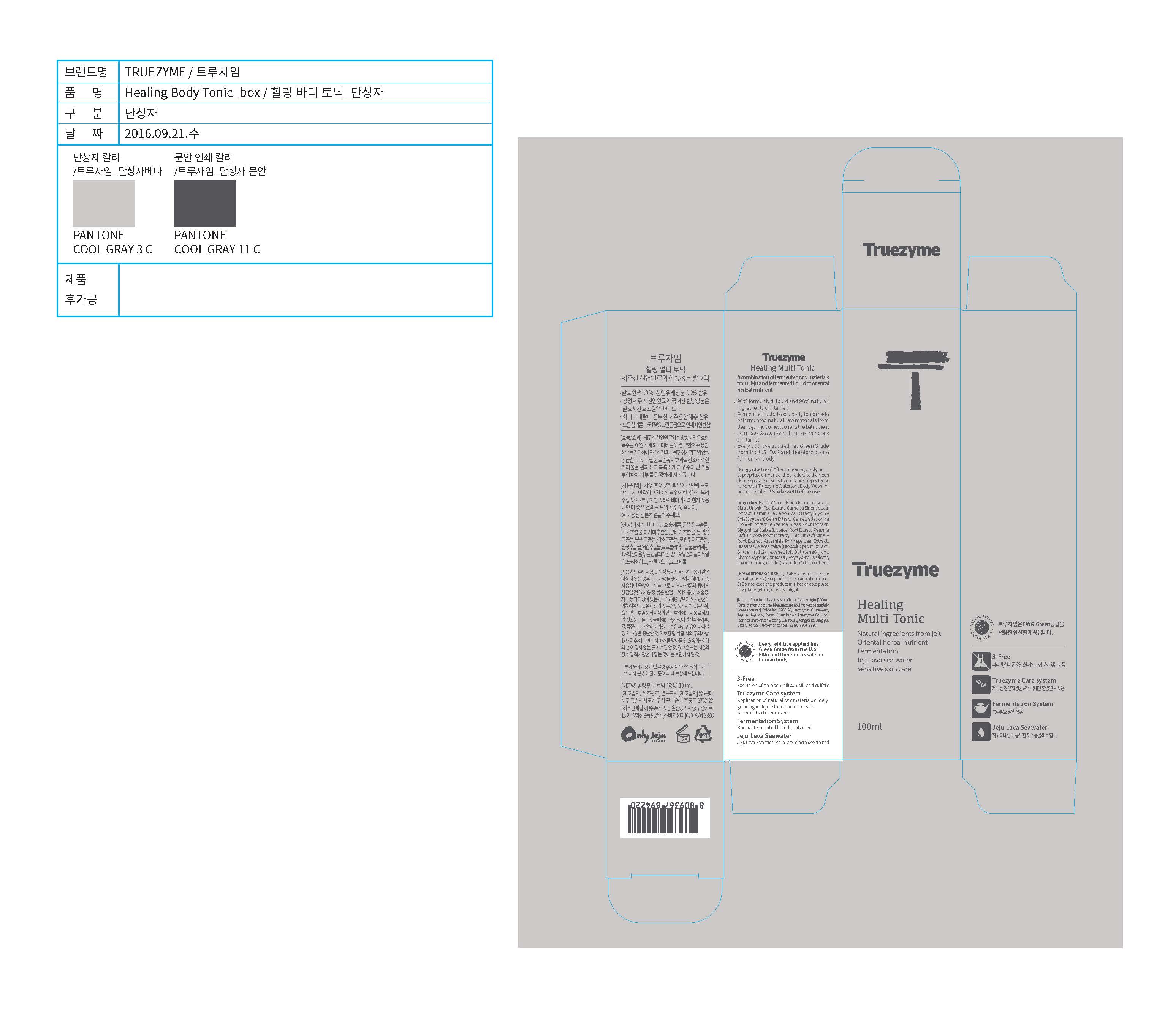 DRUG LABEL: Truezyme Healing Multi Tonic
NDC: 71076-0006 | Form: LIQUID
Manufacturer: Truezyme Co., Ltd.
Category: otc | Type: HUMAN OTC DRUG LABEL
Date: 20161227

ACTIVE INGREDIENTS: GLYCERIN 5 g/100 mL
INACTIVE INGREDIENTS: ARTEMISIA PRINCEPS LEAF OIL; GREEN TEA LEAF; CAMELLIA JAPONICA FLOWER

Drug Facts

Active ingredient

Glycerin

Purpose

Nourish the sensitive scalp and also make hair lustrous and strong

DOSAGE AND ADMINISTRATION

For external use only

INDICATIONS AND USAGE

After a shower, apply an appropriate amount of the product to the clean skin.

- Spray over sensitiv, dry area repeatedly.
- Use with Truezyme Waterlock Body Wash for better results.

* Shake well before use.

Inactive ingredients:

Camellia Japonica Flower Extract, Camellia Japonica Extract, Artemisia Princeps Leaf Extract, etc.

Keep out of reach of children.

WARNINGS

1. Make sure to close the cap after use.
2. Keep out of the reach of children.
3. Do not keep the product in a hot or cold place or a place getting direct sunlight.